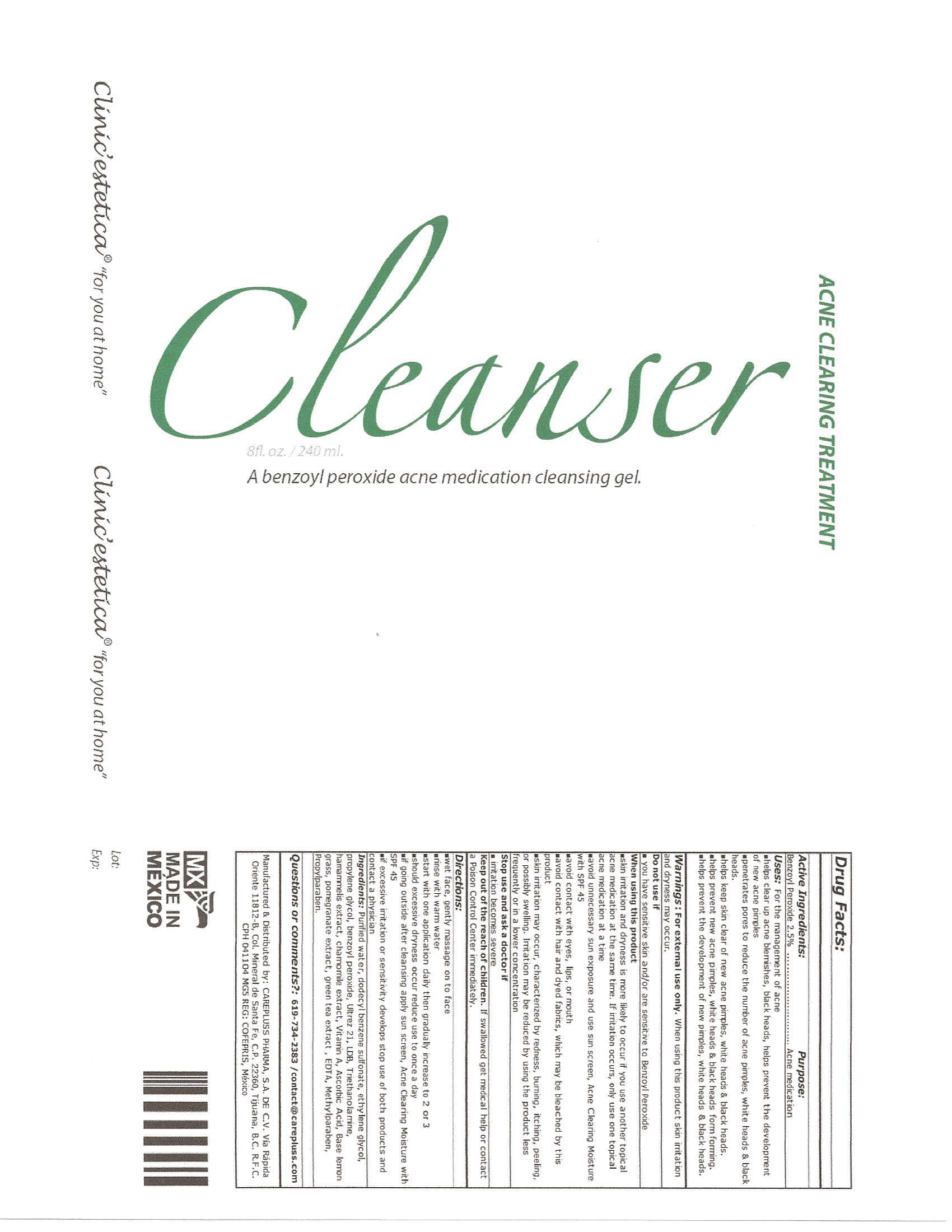 DRUG LABEL: Cleanser
NDC: 51439-005 | Form: LIQUID
Manufacturer: CarePluss Pharma S.A. de C.V.
Category: otc | Type: HUMAN OTC DRUG LABEL
Date: 20130320

ACTIVE INGREDIENTS: BENZOYL PEROXIDE .006 mg/.024 mg
INACTIVE INGREDIENTS: WATER; DODECYLBENZENESULFONIC ACID; ETHYLENE GLYCOL; PROPYLENE GLYCOL; CARBOMER COPOLYMER TYPE A (ALLYL PENTAERYTHRITOL CROSSLINKED); TROLAMINE; HAMAMELIS VIRGINIANA LEAF; CHAMAEMELUM NOBILE FLOWER; VITAMIN A; ASCORBIC ACID; WEST INDIAN LEMONGRASS OIL; POMEGRANATE; GREEN TEA LEAF; EDETIC ACID; METHYLPARABEN; PROPYLPARABEN

Active Ingredients: Purpose:
Sulphur 5%...........................................Acne medication

PURPOSE

Uses:For the management of acne

- helps clear up acne blemishes, black heads, helps prevent the development of new acne pimples
- penetrates pores to reduce the number of acne pimples, white heads and black heads
- help keep skin clear of new acne pimples, white heads and black heads
- helps prevent new acne pimples, white heads and black heads from forming
- help prevent the development of new pimples, white heads and black heads

WARNINGS

Warnings: For external use only. When using this product skin irritation and dryness may occur.
Do not use

- if you have sensitive skin and/or are sensitive to Sulphur
- on broken skin
- on skin that ha no breakouts

When using this product

- skin irritation and dryness is more likely to occur if you use another topical acne medication at the same time. If irritation occurs, only use one topical acne medication at a time
- avoid unnecessary sun exposure and use sun screen, Acne Clearing Moisture with SPL 45
- skin irritation may occur, characterized by redness, burning, itching, peeling, and possibly swelling. Irritation may be reduced by using the product less frequently or in a lower concentration

Stop use and ask a doctor if

- irritation becomes severe

Keep out of reach of children.If swallowed get medical help or contact a Poison Control center immediately.

Directions:

- cleanse skin with ACNE CLEARING CLEANSER a benzoyl peroxide acne medication cleansing gel.
- moisten fresh cotton ball with ACNE CLEARING TONIC a salicylic acid serum medication for oil control.
- apply ACNE CLEARING TREATMENT 101 a sulphur and natural anti-inflammatory lotion medication to acne breakout areas.
- start with one application daily then gradually increase to 2 or 3.
- if going outside after cleansing apply sun screen, Acne Clearing Moisture with SPF 45
- if excessive irritation or sensitivity develops stop use of both products and contact a physician.

INACTIVE INGREDIENT

Ingredients: Purified Water, Sulfer, Catalase, Aqueous extract of arnica, Glycerin, Cetyl Alcohol, Ceteareth-12, Bromelain, Ultrez 21, Mineral Oil, Ethhylene Glycol, Propylene Glycol, Sodium Ascorbyl Phosphate, Triethanolamine, Ascorbic Acid, Dodecyl Benzene Sulfonate, Peppermint oil, Piperine, Mint Base, EDTA, BHT, BHA, Methylparaben, Propylparaben.

DOSAGE AND ADMINISTRATION

2 FL OZ / 60 ml

PACKAGE LABEL

Treatment 101
Acne Clearing Treatment